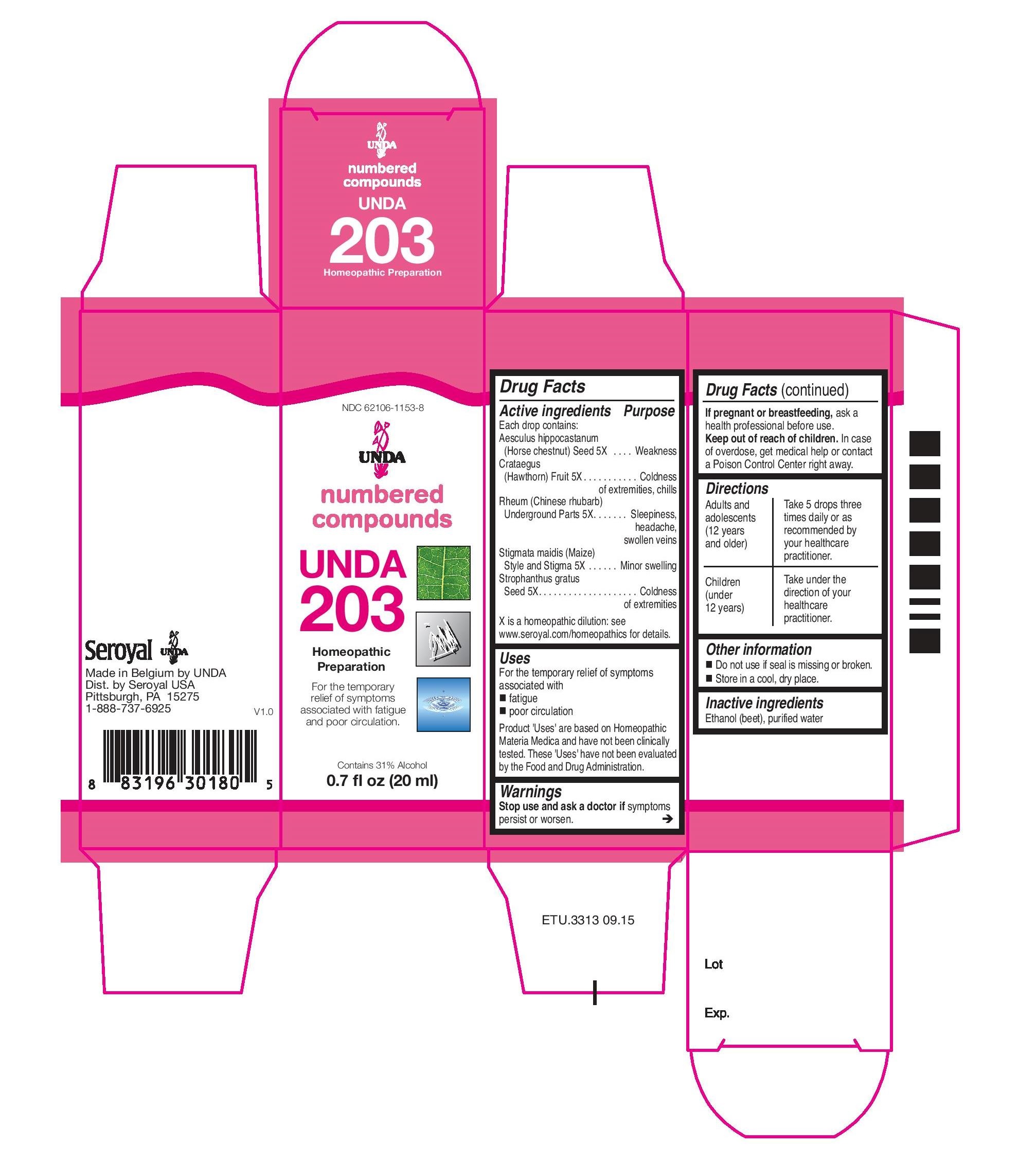 DRUG LABEL: Unda 203
NDC: 62106-1153 | Form: LIQUID
Manufacturer: Seroyal USA
Category: homeopathic | Type: HUMAN OTC DRUG LABEL
Date: 20221109

ACTIVE INGREDIENTS: CHINESE RHUBARB ROOT 5 [hp_X]/20 mL; STROPHANTHUS GRATUS SEED 5 [hp_X]/20 mL; CORN SILK 5 [hp_X]/20 mL; CRATAEGUS FRUIT 5 [hp_X]/20 mL; HORSE CHESTNUT 5 [hp_X]/20 mL
INACTIVE INGREDIENTS: ALCOHOL; WATER

Unda 203

Active ingredients

Each drop contains:
Aesculus hippocastanum (Horse chestnut) Seed 5X
Crataegus (Hawthorn) Fruit 5X
Rheum (Chinese rhubarb) Underground Parts 5X
Stigmata maidis (Maize) Style and Stigma 5X
Strophanthus gratus Seed 5X

Uses

For the temporary relief of symptoms
associated with fatigue and poor circulation

Warnings
Stop use and ask a doctor if symptoms persist or worsen.

If pregnant or breastfeeding, ask a health professional before use.
Keep out of reach of children.

In case of overdose, get medical help or contact a Poison Control Center right away.

PREGNANCY OR BREAST FEEDING

If pregnant or breastfeeding, ask a health professional before use.

Keep out of reach of children.

Other information
Do not use if seal is missing or broken.
Store in a cool, dry place.

Inactive ingredients
Ethanol (beet), purified water

Directions

Adults and adolescents (12 years and older)

Take 5 drops three times daily or as recommended by your healthcare practitioner.

Children (under 12 years)

Take under the direction of your healthcare practitioner.

Uses

For the temporary relief of symptoms associated with fatigue and poor circulation

Directions

Adults and adolescents (12 years and older)

Take 5 drops three times daily or as recommended by your healthcare practitioner.

Children (under 12 years)

Take under the direction of your healthcare practitioner.

PACKAGE LABEL

NDC 62106-1153-8

UNDA

numbered compounds

UNDA 203

Homeopathic Preparation

For the temporary relief of symptoms associated with fatigue and poor circulation.

Contains 31% Alcohol
0.7 fl oz (20 ml)